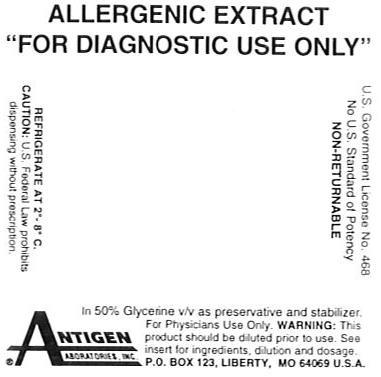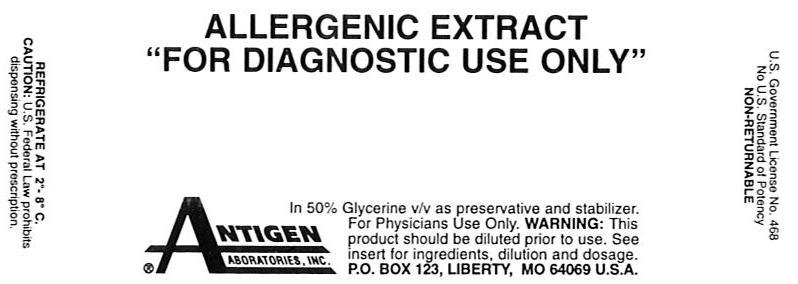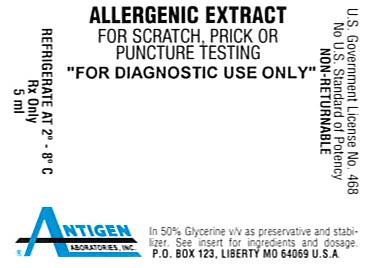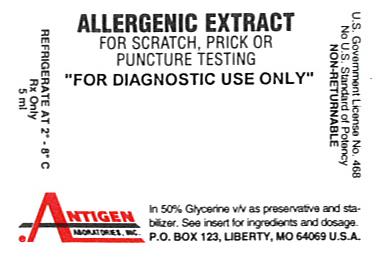 DRUG LABEL: Cricket
NDC: 49288-0160 | Form: INJECTION, SOLUTION
Manufacturer: Antigen Laboratories, Inc.
Category: prescription | Type: HUMAN PRESCRIPTION DRUG LABEL
Date: 20091112

ACTIVE INGREDIENTS: ACHETA DOMESTICUS 0.05 g/1 mL
INACTIVE INGREDIENTS: GLYCERIN 0.525 mL/1 mL; SODIUM CHLORIDE 0.0095 g/1 mL; SODIUM BICARBONATE 0.024 g/1 mL; WATER

Allergenic Extract “For Diagnostic Use Only”

WARNINGS

Allergenic extract is intended for use by physicians or under the guidance of physicians who are experienced in the administration of allergenic extracts for diagnosis and the emergency care of anaphylaxis. This extract is not directly interchangeable with other allergenic extracts. Patients should be instructed to recognize adverse reaction symptoms and cautioned to contact the physician's office if reaction symptoms occur. As with all allergenic extracts, severe systemic reactions may occur. In certain individuals, especially in steroid-dependent/unstable asthmatics, these life-threatening reactions may result in death. Patients should be observed for at least 20 minutes following testing. Emergency measures, as well as trained personnel, should be immediately available in the event of a life-threatening reaction.

This product should not be injected intravenously. See the "WARNINGS", "PRECAUTIONS", "ADVERSE REACTIONS" and "OVERDOSAGE" sections.

Sensitive patients may experience severe anaphylactic reactions resulting in respiratory obstruction, shock, coma and/or death.

Report serious adverse events to MedWatch, 5600 Fishers Lane, Rockville, MD 20852-9787, phone 1-800-FDA-1088.

Patients receiving beta-blockers may not be responsive to epinephrine or inhaled bronchodilators. Respiratory obstruction not responding to parenteral or inhaled bronchodilators may require theophylline, oxygen, intubation and the use of life support systems. Parenteral fluid and/or plasma expanders may be utilized for treatment of shock. Adrenocorticosteroids may be administered parenterally or intravenously. Refer to ''WARNINGS", "PRECAUTIONS" and "ADVERSE REACTIONS" sections below.

DESCRIPTION

Antigen Laboratories' allergenic extracts are manufactured from source material listed on the vial label. The extract is a sterile solution containing extractables of source materials obtained from biological collecting and/or processing firms. All source materials are inspected by Antigen Laboratories' technical personnel in accordance with 21 CFR 680.1 (b) (I).

The following "For Diagnostic Use Only" allergenic extracts are extracted at a 1:20 w/v or 1:50 w/v ratio of source material to extracting fluid:

The source material for Coffee is prepared by grinding the seed of the coffee plant (Coffea arabic).

The source material for Cottonseed is prepared by grinding the seed of the cotton plant (Gossypium spp.).

The source material for Flaxseed is prepared by grinding the seed of the flax plant (Linum usitatissimum).

Leafhopper source material is pulverized whole bodies of Leafhoppers (Cicadellidae).

Miller Moth source material is pulverized whole bodies of night flying moths (Lepidoptera).

Cricket source material is pulverized whole bodies of crickets (Gryllidae).

Moth source material is pulverized whole bodies of moths of the order Frenatae.

The routes of administration for diagnostic purposes are intradermal or prick-puncture of the skin.

FOR ALLERGENIC EXTRACTS CONTAINING 50% V/V GLYCERINE AS PRESERVATIVE AND STABILIZER:

INACTIVE INGREDIENTS:

Sodium chloride……………………………………………………………………...0.95%

Sodium bicarbonate………………………………………………………………….0.24%

USP Glycerine…………………………………………………………………50% (v/v)

Water for Injection…………………………………………………………q.s. to volume

Active allergens are described by common and scientific name on the stock concentrate container label.

CLINICAL PHARMACOLOGY

Studies indicate allergic individuals produce immunoglobulins of the IgE class in response to exposure to allergens. Subsequent exposure to the same allergen results in a complex of allergen with IgE antibody fixed on mast cells or basophil membranes. This cross-linking results in stimulation of mast cells which leads to release and generation of pharmacologically active substances that produce immediate hypersensitivity reaction.^1

INDICATIONS AND USAGE

FOR DIAGNOSTIC USE ONLY. This product has not been shown by adequate data to be safe and effective for therapeutic use according to Federal Register Notice dated November 16, 1994, Vol. 59, No. 220. The following allergenic extracts are "For Diagnostic Use Only": Coffee (Coffea arabic), Cottonseed (Gossypium spp.), Flaxseed (Linum usitatissimum), Leafhopper (Cicadellidae), Miller Moth (Night Flying Lepidoptera), Cricket (Gryllidae) and Moth (Frenatae). These extracts are intended for diagnostic testing of patients whose histories indicate that upon natural exposure to the allergen, they experience allergic symptoms. Confirmation is determined by skin testing.

CONTRAINDICATIONS

Do not administer in the presence of diseases characterized by bleeding diathesis. Individuals with autoimmune disease may be at risk of exacerbating symptoms of the underlying condition, possibly due to routine immunization. Children with nephrotic syndrome should not receive injections due to immunization exacerbating nephrotic diseases.

Allergenic extracts are not intended for diagnosing patients who do not manifest immediate hypersensitivity reactions to the allergenic extract when skin tested.

WARNINGS

Extreme caution is necessary when using diagnostic skin tests in highly sensitive patients who have experienced severe symptoms or anaphylaxis by natural exposure or previous skin testing or treatment. IN THESE CASES THE POTENCY FOR SKIN TESTS MUST BE ADJUSTED TO THE PATIENT'S SENSITIVITY AND TOLERANCE. Refer to boxed “WARNINGS" and “OVERDOSAGE" sections.

Epinephrine 1:1000 should be available when a new lot of allergenic extract is utilized. Patient re-evaluation may be necessary. Injections should never be given intravenously. Adverse reactions to allergenic extracts are usually apparent within 20-30 minutes following skin testing. Patients should be observed for 20-30 minutes after skin testing.

PRECAUTIONS

General:

Sterile solutions, vials, syringes, etc. must be used. Aseptic technique should be observed in making dilutions for skin testing.

DO NOT INJECT INTRAVENOUSLY

Observe caution in making test injection to minimize adverse reactions. The usual precautions in administering allergenic extracts are necessary (refer to boxed "WARNINGS" and "OVERDOSAGE" sections). A disposable, sterile syringe and needle should be used for each individual patient to prevent transmission of serum hepatitis, Human Immunodeficiency Virus (HIV) and other infectious agents.

It cannot be overemphasized that, under certain unpredictable combinations of circumstances, anaphylactic shock is always a possibility. Other possible systemic reaction symptoms are, in varying degrees of severity: fainting, pallor, bradycardia, hypotension, angioedema, cough, wheezing, conjunctivitis, rhinitis, and urticaria.^4,5

With careful attention to administration, such reactions occur infrequently, but it must be remembered that allergenic extracts are highly potent to sensitive individuals and overdose could result in anaphylactic symptoms. Therefore, it is imperative that physicians administering allergenic extracts understand and be prepared for the treatment of severe reactions.

Refer to "OVERDOSAGE" section for a description of the treatment of anaphylactic reactions.

Information for Patients:

Patients should remain under observation of nurse, physician, or other personnel trained in emergency measures for at least 20 minutes following testing. Any adverse reactions during or after leaving the office should be reported to the physician or their qualified personnel.

Carcinogenesis, Mutagenesis, Impairment of Fertility:

Long term studies in animals have not been conducted with allergenic extract to determine their potential for carcinogenicity, mutagenicity or impairment of fertility.

Pregnancy Category C:

Animal reproduction studies have not been conducted with allergenic extracts. It is not known whether allergenic extracts cause fetal harm during pregnancy or affect reproductive capacity. A systemic reaction to allergenic extract could cause uterine contractions leading to spontaneous abortion or premature labor. Allergenic extracts should be used during pregnancy only if potential benefit justifies potential risk to fetus.^3

Nursing Mothers:

It is not known whether allergenic extracts are excreted in human milk. Because many drugs are excreted in human milk, caution should be exercised when allergenic extracts are administered to a nursing woman.

Pediatric Use:

Allergenic extracts have been used routinely in children, and no special safety problems or specific hazards have been found.^7,8

Drug Interactions:

Antihistamines. Antihistamines inhibit the wheal and flare reaction. The inhibitory effect of conventional antihistamines varies from 1 day up to 10 days, according to the drug and patient's sensitivity. Long acting antihistamines (e.g., astemizole) may inhibit the wheal and flare for up to forty days.

Imipramines, phenothiazines, and tranquilizers. Tricyclic antidepressants exert a potent and sustained decrease of skin reactions to histamine that may last for a few weeks. Tranquilizers and antiemetic agents of the phenothiazine class have H1 antihistaminic activity and can block skin tests.^2

Corticosteroids. Short-term (less than 1 week) administration of corticosteroids at the therapeutic doses used in asthmatic patients does not modify the cutaneous reactivity to histamine, compound 48/80, or allergen. Long-term corticosteroid therapy modifies the skin texture and makes the interpretation of immediate skin tests more difftcult.^2

Theophylline. It appears that theophylline need not be stopped prior to skin testing. ^2

Beta-adrenergic agents. Inhaled beta2 agonists in the routine doses for the treatment of asthma do not usually inhibit allergen-induced skin tests. However, oral terbutaline and parenteral ephedrine were shown to decrease the allergen-induced wheal.^2

Cromolyn. Cromolyn inhaled or injected prior to skin tests with allergens or degranulating agents does not alter the skin whealing response.^2

Other drugs. Other drugs have been shown to decrease skin test reactivity. Among them, dopamine is the best-documented compound.^2

ADVERSE REACTIONS

Adverse reactions include, but are not necessarily limited to urticaria, itching, edema of the extremities, respiratory wheezing or asthma, dyspnea, cyanosis, tachycardia, lacrimation, marked perspiration, flushing of the face, neck or upper chest, mild persistent clearing of the throat, hacking cough or persistent sneezing.

1) Local Reactions

A small amount of erythema and swelling at the site of injection is common, the extent varying with the patient. Such reactions should not be considered significant unless they persist for at least 24 hours or exceed 50 mm in diameter.

Large, persistent local reactions or minor exacerbations of the patient's allergic symptoms may be treated by local cold applications and/or the use of oral antihistamines, but they should be considered a warning of possible severe systemic reactions.

A mild burning immediately after the injection is to be expected; this usually is relieved in 10-20 seconds.

2) Systemic Reactions

Systemic reactions may range from mild exaggeration of the patient's allergic symptoms to anaphylactic reactions. Very sensitive patients may show a rapid response. In some instances, a severe systemic reaction with blood pressure fall and/or shock may occur. Quantitation of patient's sensitivity combined with careful early observation is essential for safe skin testing.^9

Patients receiving beta-blockers may not be responsive to epinephrine or inhaled bronchodilators. The following are commonly prescribed beta-blockers: Levatol, Lopressor, Propanolol Intersol, Propanolol HCL, Blocadren, Propanolol, Inderal-LA, Visken, Corgard, Ipran, Tenormin, Timoptic. Ophthalmic beta-blockers: Betaxolol, Levobunolol, Timolol, Timoptic. Chemicals that are beta-blockers and may be components of other drugs: Acebutolol, Atenolol, Esmolol, Metoprolol, Nadolol, Penbutolol, Pindolol, Propanolol, Timolol, Labetalol, Carteolol.

OVERDOSAGE

Refer to “WARNINGS," "PRECAUTIONS" and "ADVERSE REACTIONS" sections for signs and symptoms of an overdose.

If a systemic or anaphylactic reaction does occur, the first treatment should be injection intramuscularly or subcutaneously 0.3 to 0.5 ml of 1:1000 epinephrine-hydrochloride into the opposite arm or gluteal area. Apply tourniquet above site of allergenic extract injection and loosen briefly at 5 minute intervals to prevent circulatory impairment. If oxygen is indicated, it may be administered by nasal cannula or ambu bag.

The epinephrine HCL 1:1000 dose for infants to 2 years is 0.05 to 0.1 ml; for children 2 to 6 years it is 0.15 ml; for children 6 to 12 years it is 0.2 ml.

Symptoms of progressive anaphylaxis include airway obstruction and/or vascular collapse.

After administration of epinephrine, profound shock and vasomotor collapse should be treated with intravenous fluids and possibly vasoactive drugs. Monitor airways for obstruction. Oxygen should be given by mask if indicated.

Antihistamines, H2 antagonist, bronchodilators, steroids and theophylline may be used as indicated after giving adequate epinephrine and circulatory support.^6

Patients who have been taking a beta-blocker may be unresponsive to epinephrine. Epinephrine or beta-adrenergic drugs (Alupent) may be ineffective. These drugs should be administered even though a beta-blocker may have been taken. The following treatment will be effective whether or not patient is taking a beta-blocker: Aminophylline IV, slow push or drip, Atrovent (Ipratropium bromide) Inhaler, 3 inhalations repeated, Atropine, 0.4 mg/ml, 0.75 to 1.5 ml IM or IV, Solu-Cortef, 100-200 mg IM or IV, Solu-Medrol, 125 mg IM or IV, Glucagon, 0.5-1 mg IM or IV, Benadryl, 50 mg IM or IV, Cimetidine, 300 mg IM or IV, Oxygen via ambu bag.

DOSAGE AND ADMINISTRATION

Parenteral drug products should be inspected visually for particulate matter and discoloration prior to administration, whenever solution and container permit. Some allergenic extracts naturally precipitate. This allergenic extract is "For Diagnostic Use Only". (Refer to STORAGE section.)

PRICK-PUNCTURE TESTING: To identify highly sensitive individuals and as a safety precaution, it is recommended that a prick-puncture test using a drop of the extract concentrate be performed prior to initiating very dilute intradermal testing. Prick-puncture testing is performed by placing a drop of extract concentrate on the skin and puncturing the skin through the drop with a small needle such as a bifurcated vaccinating needle. The most satisfactory sites on the back for skin testing are from the posterior axillary fold to 2.5 cm from the spinal column, and from the top of the scapula to the lower rib margins. The best areas on the arms are the volar surfaces from the axilla to 2.5 or 5 cm above the wrist, skipping the anticubital space. Skin testing should include a positive control of histamine phosphate and a negative control of 50% v/v glycerine in buffered saline. A positive reaction is approximately 10-15 mm erythema with 2.5 mm wheal. Smaller, less conclusive reactions may be considered positive in conjunction with a definitive history of symptoms on exposure to the allergen. Less sensitive individuals can be tested intradermally with an appropriately diluted extract (See "INTRADERMAL TESTING").

INTRADERMAL TESTING: The surface of the upper and lower arm is the usual location for skin testing. A sterile, disposable syringe and needle is used for each extract tested. Intracutaneous test dilutions, five-fold or ten-fold, may be prepared from stock concentrate using physiologic saline as a diluent. (1) Start testing with the most dilute allergenic extract concentration. (2) A volume of 0.02-0.05 ml should be injected slowly into the superficial skin layers making a small bleb (superficial wheal). (3) For patients without a history of extreme sensitivity, or a negative or weakly reactive prick-puncture test, the initial dilution for skin testing should be at least 1:12,500 w/v. This initial dilution can be prepared by diluting 1:20 to 1:50 w/v (2%-5%) extracts five-fold to 5^-4 or 1:10 w/v (10%) extracts to 5^-5. Dilute 1:10 w/v (10%) extracts to 10^-3 if using ten-fold dilutions. (4) Sensitive patients with a positive prick-puncture test require a further dilution to at least 1:312,500 w/v. This dilution can be prepared by diluting 1:20 to 1:50 w/v (2%-5%) extracts to 5^-6 or 1:10 w/v (10%) extracts to 5^-7 (five-fold dilutions). Ten-fold dilution to 10^-6 of a 1:10 w/v (10%) extract would be a safe starting dilution. For interpretation of skin reactions, refer to chart below. If after 20 minutes no skin reaction is observed, continue testing using increasing increments of the concentration until a reaction of 5-10 mm wheal and 11-30 mm erythema is obtained, or a concentration of 5^-2 or 10^-1 has been tested. A negative control, 50% glycerine diluted with diluent to 5^-2 (1:25) or 10^-1 (1:10) dilution and a positive control of histamine phosphate, should be tested and included in interpretation of skin reactions.^2,4

GRADE | mm ERYTHEMA | mm WHEAL
0 | less than 5 | less than 5
± | 5-10 | 5-10
1+ | 11-20 | 5-10
2+ | 21-30 | 5-10
3+ | 31-40 | 10-15 or with pseudopods
4+ | greater than 40 | greater than 15 or with many pseudopods

INTRADERMAL TESTING–SKIN ENDPOINT TITRATION: The allergenic extracts to which the patient is sensitive and the patient's degree of sensitivity can be determined through the use of intracutaneous skin tests involving progressive five-fold dilutions of allergenic extracts. Intracutaneously inject 0.01 to 0.02 ml of the test allergen to form a 4 mm diameter superficial skin wheal. For patients demonstrating a negative or weakly reactive prick-puncture skin test, an initial screening dilution of 1:12,500 w/v is safe. For patients demonstrating a positive prick-puncture skin test, an initial screening dilution of 1:312,500 w/v is safe (see "Serial Dilution Titration Test Dilutions" chart below).When a sequence of five-fold or ten-fold dilutions of an allergen is injected, the endpoint is determined by noting the dilution that first produces a wheal or erythema (15 minutes after injection) that is 2 mm larger than wheals with erythema produced by weaker, non-reacting dilutions (5 mm negative wheal).

SERIAL DILUTION TITRATION TEST DILUTIONS APPROXIMATE ALLERGENIC EXTRACT CONCENTRATION RESULTING FROM 1:5 DILUTION
Titration Number | Dilution Exponent | Weight / Volume | Allergenic Extract Concentrate
Titration Number | Dilution Exponent | Weight / Volume | 1:50 (2%) | 1:40 (2 1/2%) | 1:33 1/3 (3%) | 1:20 (5%) | 1:10 (10%)
No. 1 | 5^-1 | 1:5 | 1:250 | 1:200 | 1:167 | 1:100 | 1:50
No. 2 | 5^-2 | 1:25 | 1:1,250 | 1:1,000 | 1:835 | 1:500 | 1:250
No. 3 | 5^-3 | 1:125 | 1:6,250 | 1:5,000 | 1:4,175 | 1:2,500 | 1:1,250
No. 4 | 5^-4 | 1:625 | 1:31,250 | 1:25,000 | 1:20,875 | 1:12,500 | 1:6,250
No. 5 | 5^-5 | 1:3,125 | 1:156,250 | 1:125,000 | 1:104,375 | 1:62,500 | 1:31,250
No. 6 | 5^-6 | 1:15,625 | 1:781,250 | 1:625,000 | 1:521,875 | 1:312,500 | 1:156,250
No. 7 | 5^-7 | 1:78,125 | 1:3,906,250 | 1:3,125,000 | 1:2,609,375 | 1:1,562,500 | 1:781,250
No. 8 | 5^-8 | 1:390,625 | 1:19,531,250 | 1:15,625,000 | 1:13,046,875 | 1:7,812,500 | 1:3,906,250
No. 9 | 5^-9 | 1:1,953,125 | 1:97,656,250 | 1:78,125,000 | 1:65,234,375 | 1:39,062,500 | 1:19,531,250
No. 10 | 5^-10 | 1:9,765,625 | 1:488,281,250 | 1:390,625,000 | 1:326,171,875 | 1:195,312,500 | 1:97,656,250
No. 11 | 5^-11 | 1:48,828,125 | 1:2,441,406,250 | 1:1,953,125,000 | 1:1,630,859,375 | 1:976,562,500 | 1:488,281,250
No. 12 | 5^-12 | 1:244,140,625 | 1:12,207,031,250 | 1:9,765,625,000 | 1:8,154,296,875 | 1:4,882,812,500 | 1:2,441,406,250

HOW SUPPLIED

The stock concentrate of allergenic extract is expressed in weight/volume, at 1:50 w/v (2%) or 1:20 w/v (5%). It is supplied in 10, 30 and 50 ml containers. Extracts in 5 ml sterile dropper bottles are available for prick-puncture testing. To insure maximum potency for the entire dating period, all stock concentrates contain 50% glycerine v/v.

STORAGE

Store all stock concentrates and dilutions at 2-8 degrees C and keep at this temperature during office use. The expiration date of the allergenic extract is listed on the container label. Dilutions of the allergenic extract concentration containing less then 50% glycerine are less stable. If loss of potency is suspected, potency can be checked using side by side skin testing with freshly prepared dilutions of equal concentration on individuals with known sensitivity to the allergen.

REFERENCES

1. Holgate, S.T., Robinson, C., Church, Mike: Mediators of Immediate Hypersensitivity, Third Edition, Allergy Principles and Practice, C.V. Mosby Co., Vol. I and II, pp 135-163, 1988.

2. Bousquet, Jean: "In vivo methods for study of allergy: Skin tests" Third Edition, Allergy Principles and Practice, C.V. Mosby Co., Vol. I and II, pp. 419-436, 1988.

3. Seebohm, P.M., et al: Panel on Review of Allergenic Extracts, Final Report, Food and Drug Administration, March 13, 1981, pp. 9-48.

4. Van Metre, T., Adkinson, N., Amodio, F., Lichtenstein, L., Mardinay, M., Norman, P., Rosenberg, G., Sobotka, A., Valentine, M.: "A Comparative Study of the Effectiveness of the Rinkel Method and the Current Standard Method of Immunology for Ragweed Pollen Hay Fever," The Journal of Clinical Allergy and Immunology, Vol. 66, No. 6, pg. 511, December 1980.

5. Wasserman, S.: The Mast Cell and the Inflammatory Response. The Mast CeIl–its role in health and disease. Edited by J. Pepys & A.M. Edwards, Proceedings of an International Symposium, Davos, Switzerland, Pitman Medical Publishing Co., 1979, pp. 9-20.

6. Wasserman, S., Marquart, D.: Anaphylaxis, Third Edition, Allergy Principles and Practice, Vol. I, Chapter 58, p. 1365, edited by Middleton et al.

7. Bullock, J., Frick, O.: Mite Sensitivity in House Dust Allergic Children, Am. J. Dis. Child.,pp. 123-222,1972.

8. Willoughby, J.W.: Inhalant Allergy Immunotherapy with Standardized and Nonstandardized Allergenic Extracts, American Academy of Otolaryngology-Head and Neck Surgery:

Instructional Courses, Vol. 1, Chapter 15, C.V. Mosby Co., St. Louis, Missouri, September 1988.

9. Reid, Michael J., Lockey, Richard F., Turkeltaub M.D., Paul C., Platts-Mills, Thomas: "Survey of Fatalities From Skin Testing and Immunotherapy 1985-1989," Journal of Allergy and Clinical Immunology, Vol. 92, No.1, pp. 6-15, 1993.